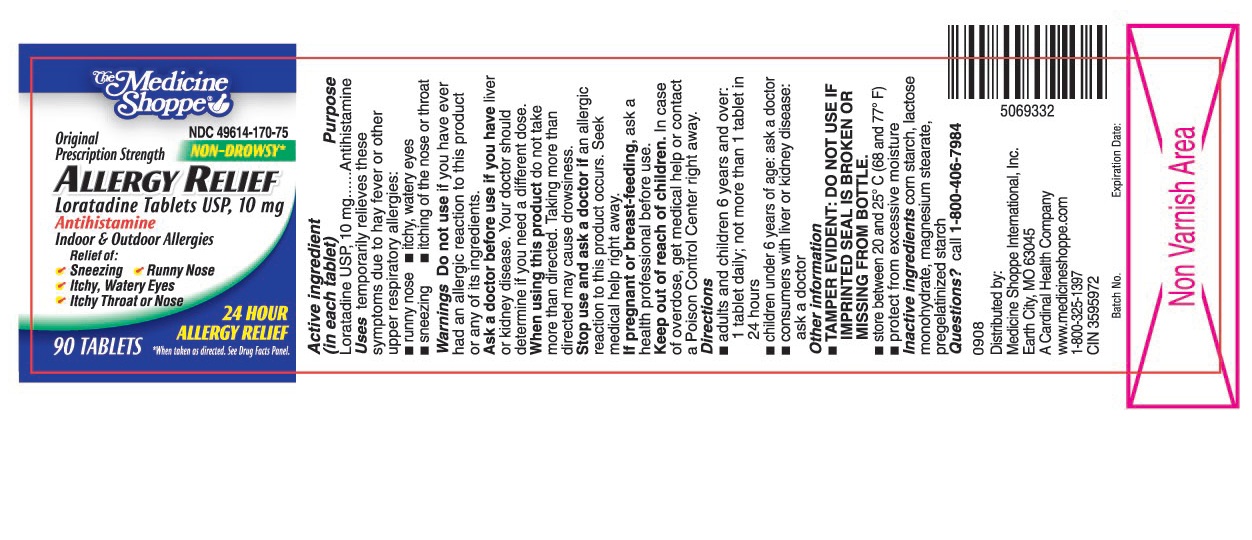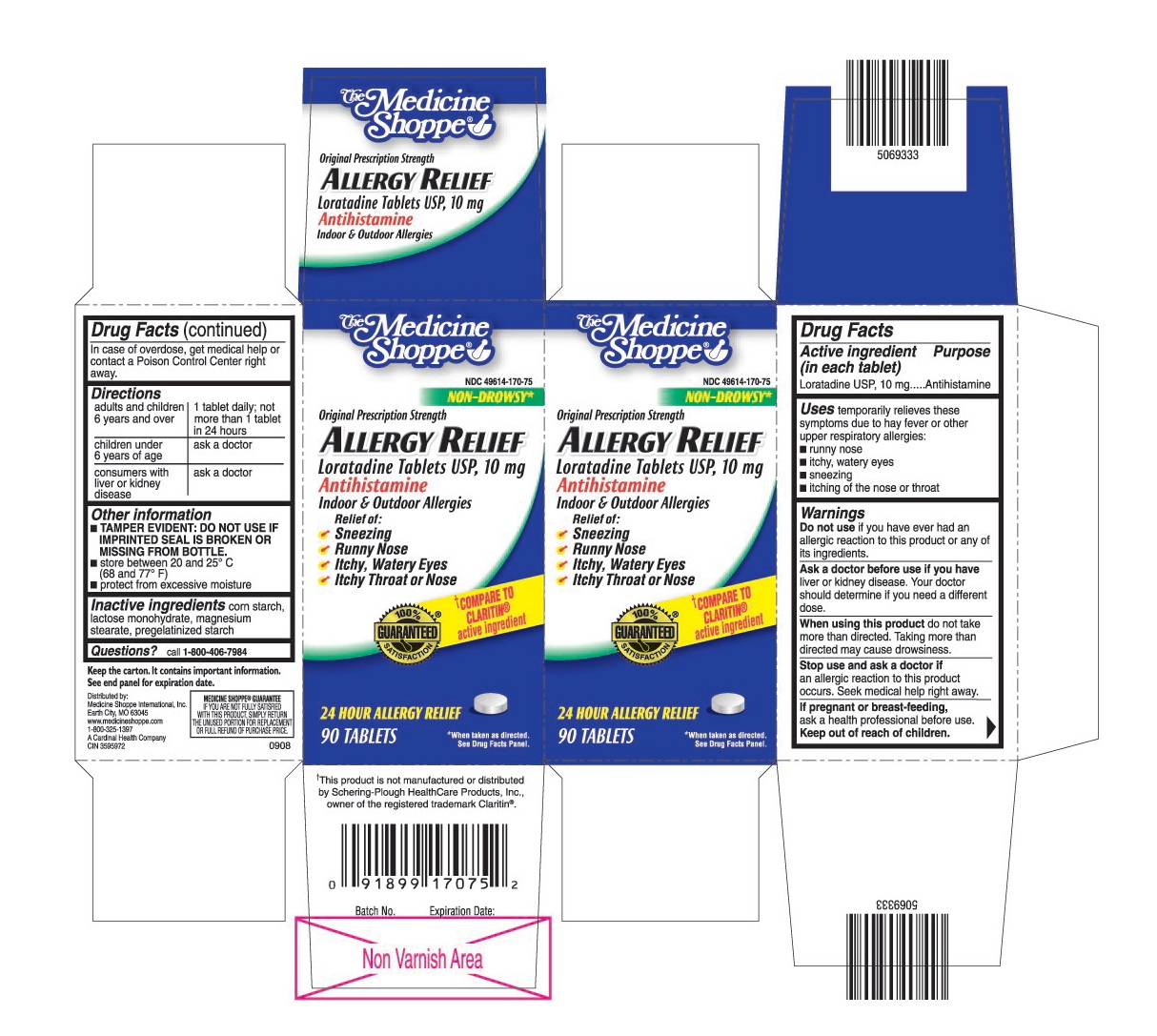 DRUG LABEL: Medicine Shoppe Loratadine Allergy Relief
NDC: 49614-170 | Form: TABLET
Manufacturer: The Medicine Shoppe International
Category: otc | Type: HUMAN OTC DRUG LABEL
Date: 20120413

ACTIVE INGREDIENTS: LORATADINE 10 mg/1 1
INACTIVE INGREDIENTS: LACTOSE MONOHYDRATE; MAGNESIUM STEARATE; STARCH, CORN; STARCH, PREGELATINIZED CORN

Drug Facts

ACTIVE INGREDIENT (IN EACH TABLET)

Loratadine USP, 10 mg

PURPOSE

Antihistamine

USES

temporarily relieves these symptoms due to hay fever or other upper respiratory allergies:

- runny nose
- itchy, watery eyes
- sneezing
- itching of the nose or throat

WARNINGS

Do not use

if you have ever had an allergic reaction to this product or any of its ingredients.

Ask a doctor before use if you have

liver or kidney disease. Your doctor should determine if you need a different dose.

When using this product

do not take more than directed. Taking more than directed may cause drowsiness.

Stop use and ask a doctor if

an allergic reaction to this product occurs. Seek medical help right away.

If pregnant or breast-feeding

ask a health professional before use.

Keep out of reach of children

In case of overdose, get medical help or contact a Poison Control Center right away.

DIRECTIONS

adults and children 6 years and over: 1 tablet daily; not more than 1 tablet in 24 hours

children under 6 years of age: ask a doctor

consumers with liver or kidney disease: ask a doctor

OTHER INFORMATION

- TAMPER EVIDENT: DO NOT USE IF BLISTER UNITS ARE TORN, BROKEN OR SHOW ANY SIGNS OF TAMPERING.
- TAMPER EVIDENT: DO NOT USE IF IMPRINTED SEAL IS BROKEN OR MISSING FROM BOTTLE.
- store between 20 and 25° C (68 and 77° F)
- protect from excessive moisture

INACTIVE INGREDIENTS

corn starch, lactose monohydrate, magnesium stearate, pregelatinized starch

QUESTIONS?

call 1-800-406-7984

Keep the carton. It contains important information.

See end panel for expiration date.

Distributed by

Medicine Shoppe International, Inc.

Earth City, MO 63045

www.medicineshoppe.com

1800-325-1397

PRINCIPAL DISPLAY PANEL

The Medicine Shoppe®

NDC 49614-170-75

Non-Drowsy*

Original Prescription Strength

Loratadine Tablets USP, 10 mg

Antihistamine

Indoor & Outdoor Allergies

24 Hour Allergy Relief

Relief of:

Sneezing

Runny Nose

Itchy, Watery Eyes

Itchy Throat or Nose

* When taken as directed. See Drug Facts Panel.

90 TABLETS

Compare to Claritin® active ingredient†

† This product is not manufactured or distributed by Schering-Plough HealthCare Products, Inc., owner of the registered trademark Claritin®.